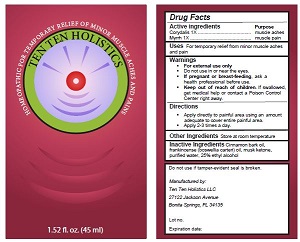 DRUG LABEL: Tincture
NDC: 62266-3246 | Form: LIQUID
Manufacturer: ChangShu Starsea pharmaceutical Co., Ltd
Category: homeopathic | Type: HUMAN OTC DRUG LABEL
Date: 20170303

ACTIVE INGREDIENTS: DICENTRA CANADENSIS ROOT 1 [hp_X]/100 mL; MYRRH 1 [hp_X]/100 mL
INACTIVE INGREDIENTS: FRANKINCENSE; CINNAMON OIL; MUSK KETONE

PURPOSE

For Muscle pain and aches

ACTIVE INGREDIENTS

CORYDALIS 1X

MYRRH 1X

INDICATIONS AND USAGE

For temporary relief of minor muscle aches
and pain

Warnings

For external use only
Do not use in or near the eyes.
If pregnant or breast-feeding, ask a health professional before use.

Keep out of reach of children.

If swallowed, get medical help or contact a Poison Control Center right away

Directions
Apply directly to painful area using an amount adequate to cover entire painful area.
Apply 2-3 times a day.

Inactive Ingredients Cinnamon bark oil,
frankincense (boswellia carteri) oil, musk ketone,
purified water, 25% ethyl alcohol

OTHER SAFETY INFORMATION

Store at room temperature